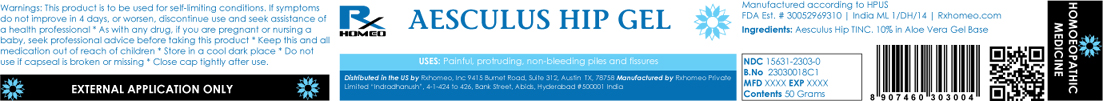 DRUG LABEL: AESCULUS HIP
NDC: 15631-2303 | Form: GEL
Manufacturer: Rxhomeo Private Limited d.b.a. Rxhomeo, Inc
Category: homeopathic | Type: HUMAN OTC DRUG LABEL
Date: 20191220

ACTIVE INGREDIENTS: HORSE CHESTNUT 1 [hp_X]/1 g
INACTIVE INGREDIENTS: ALOE VERA LEAF

ACTIVE INGREDIENT

AESCULUS HIPPOCASTANUM TINC HPUS

USES

Painful, protruding, non-bleeding piles and fissures

INDICATIONS

Condition listed above or as directed by the physician

DOSAGE & ADMINISTRATION SECTION

Apply a thin layer of Gel to the affected area, repeat 3 times a day or as needed.

WARNINGS

This product is to be used for self-limiting conditions

STOP USE

If symptoms do not improve in 4 days, or worsen, discontinue use and seek assistance of health professional

PREGNANCY OR BREAST FEEDING

As with any drug, if you are preganant, or nursing a baby, seek professional advice before taking this product

KEEP OUT OF REACH OF CHILDREN

Keep this and all medication out of reach of children

Do not use if capseal is broken or missing.
Close the cap tightly after use.

INACTIVE INGREDIENTS

ALOE VERA GEL

STORAGE

Store in a cool dark place

QUESTIONS OR COMMENTS

www.Rxhomeo.com | 1.888.2796642 | info@rxhomeo.com

Rxhomeo, Inc 9415 Burnet Road, Suite 312, Austin, TX 78758